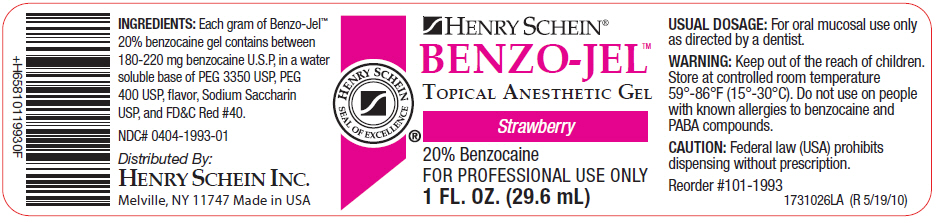 DRUG LABEL: Benzo-Jel 
NDC: 0404-1993 | Form: GEL
Manufacturer: Henry Schein Inc
Category: prescription | Type: HUMAN PRESCRIPTION DRUG LABEL
Date: 20150501

ACTIVE INGREDIENTS: Benzocaine 230 mg/1 mL

BENZO-JEL™

INGREDIENTS

Each gram of Benzo-Jel™ 20% benzocaine gel contains between 180-220 mg benzocaine U.S.P, in a water soluble base of PEG 3350 USP, PEG 400 USP, flavor, Sodium Saccharin USP, and FD&C Red #40.

USUAL DOSAGE

For oral mucosal use only as directed by a dentist.

WARNING

Keep out of the reach of children. Store at controlled room temperature 59°-86°F (15°-30°C). Do not use on people with known allergies to benzocaine and PABA compounds.

CAUTION

Federal law (USA) prohibits dispensing without prescription.

Reorder #101-1993

1731026LA (R 5/19/10)

NDC# 0404-1993-01

Distributed By:
HENRY SCHEIN INC.
Melville, NY 11747 Made in USA

PRINCIPAL DISPLAY PANEL - 29.6 mL Jar Label

HENRY SCHEIN®

BENZO-JEL™
TOPICAL ANESTHETIC GEL

Strawberry

20% Benzocaine
FOR PROFESSIONAL USE ONLY
1 FL. OZ. (29.6 mL)

HENRY SCHEIN
SEAL OF EXCELLENCE®